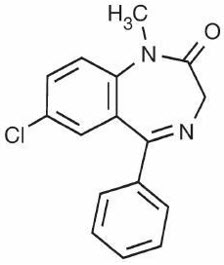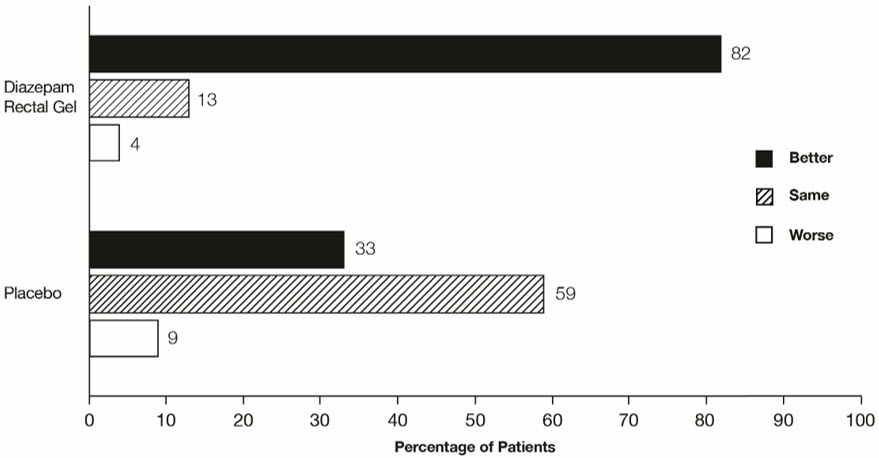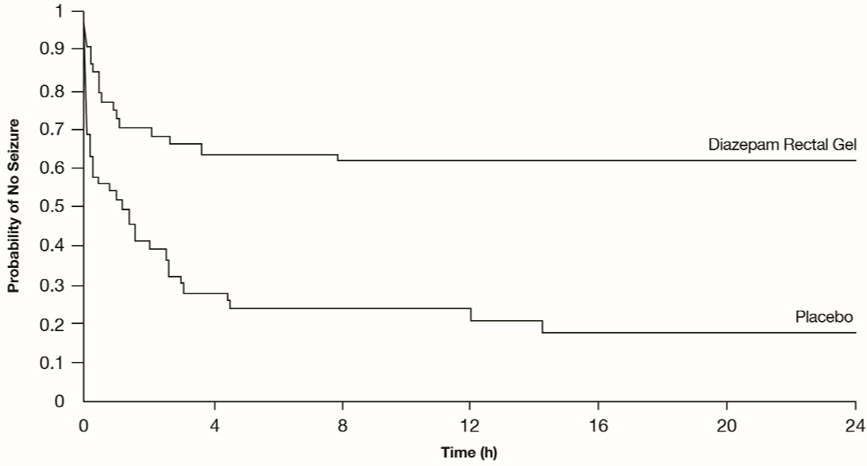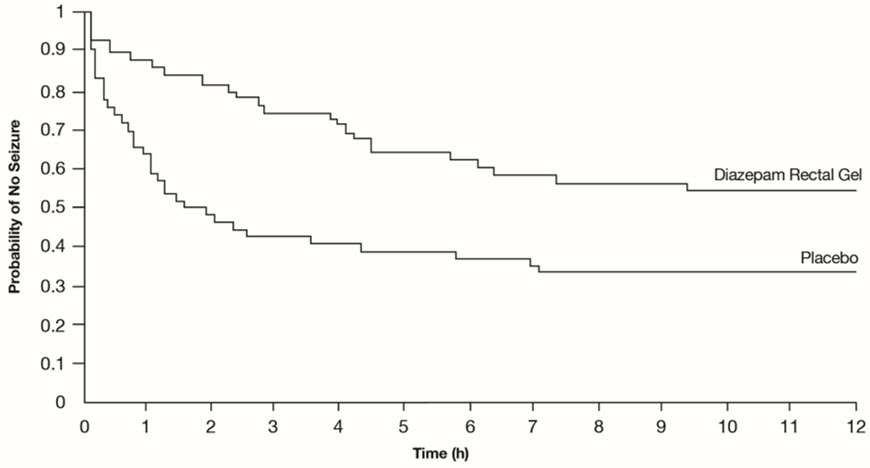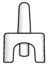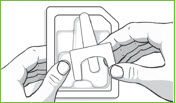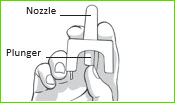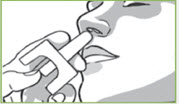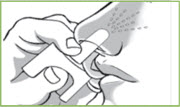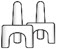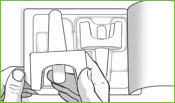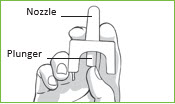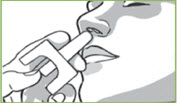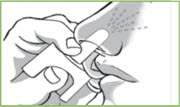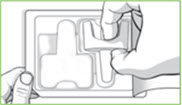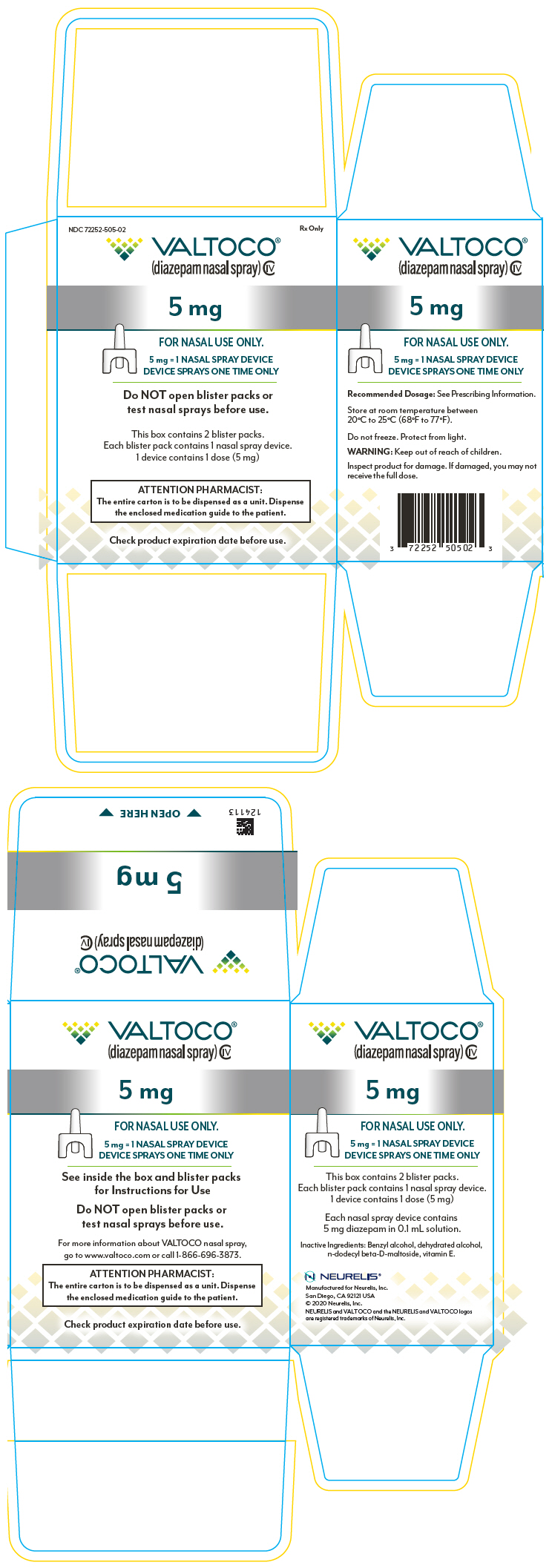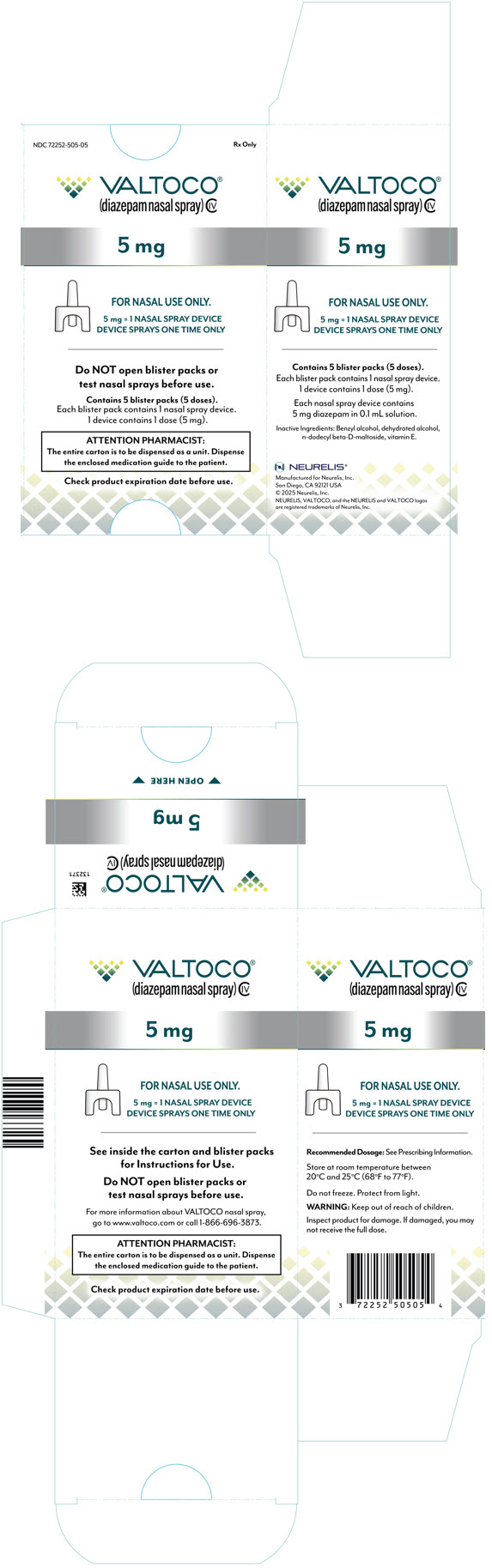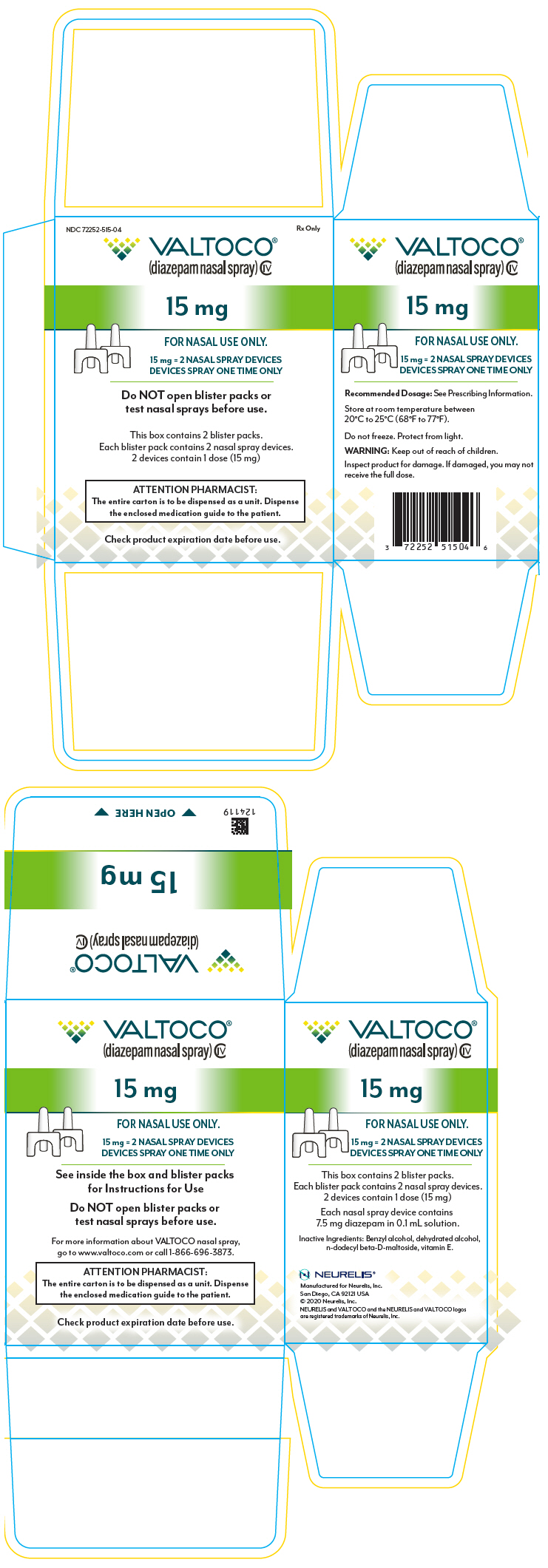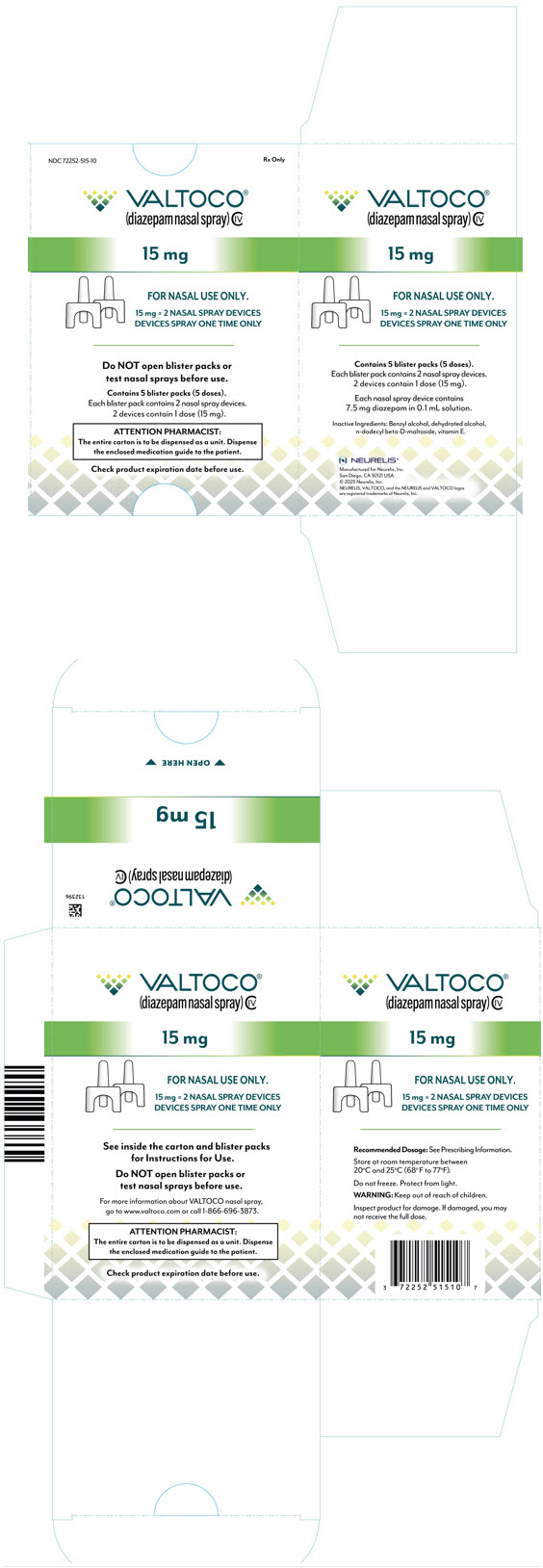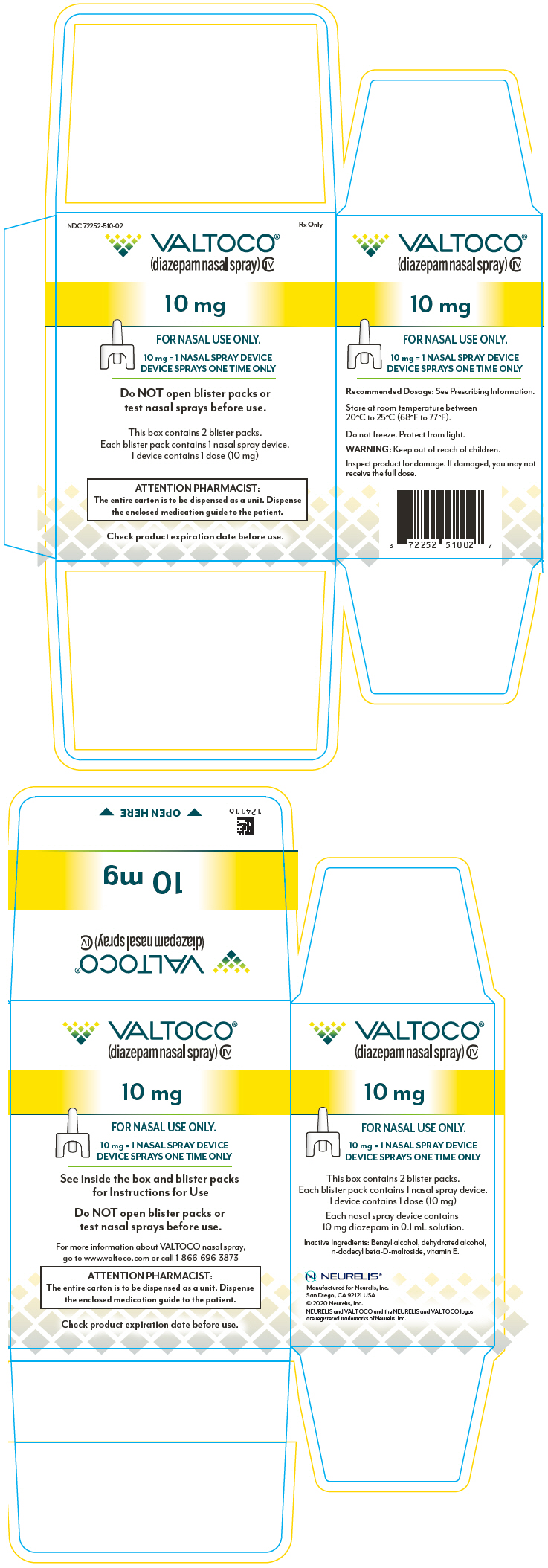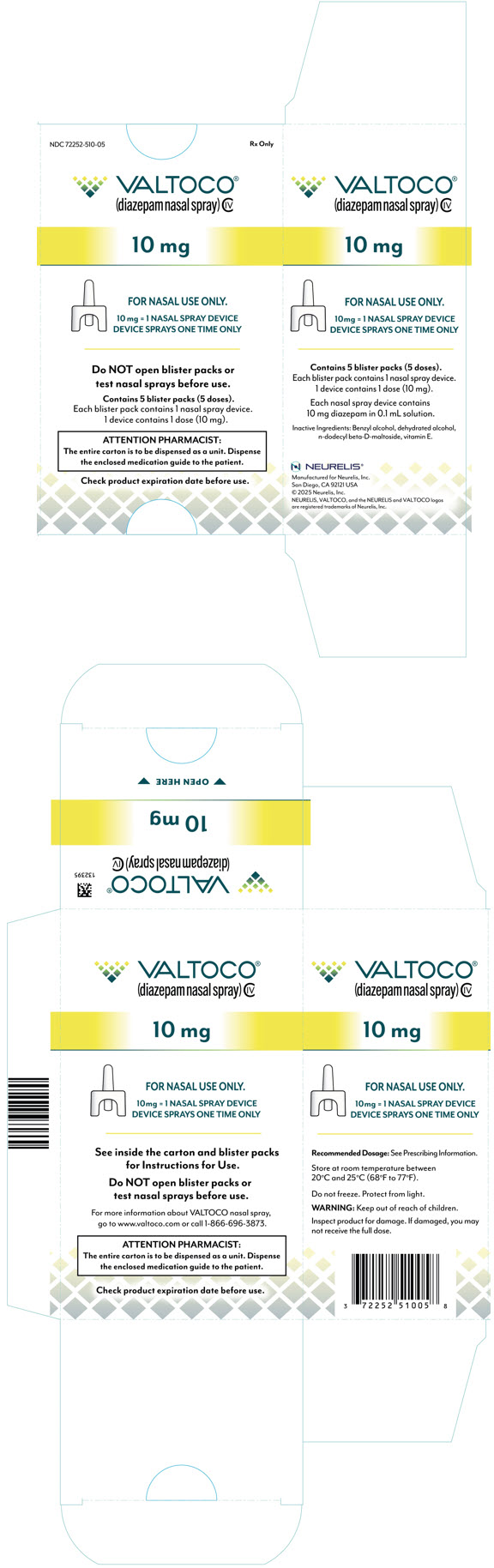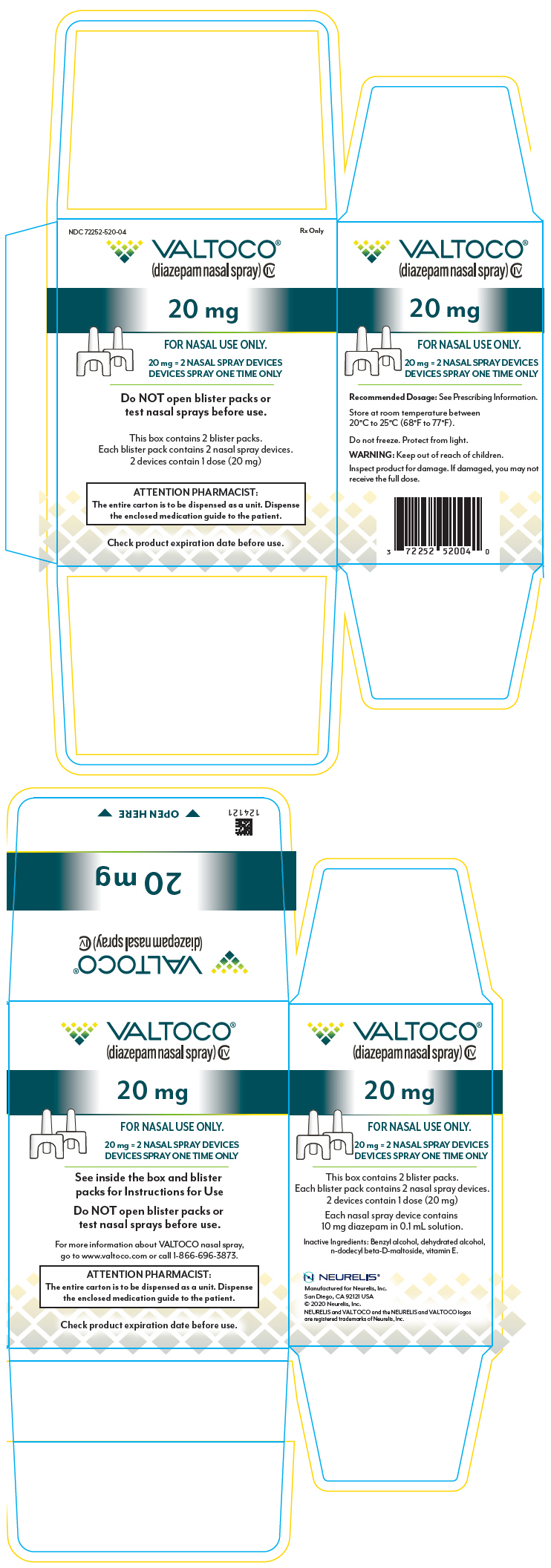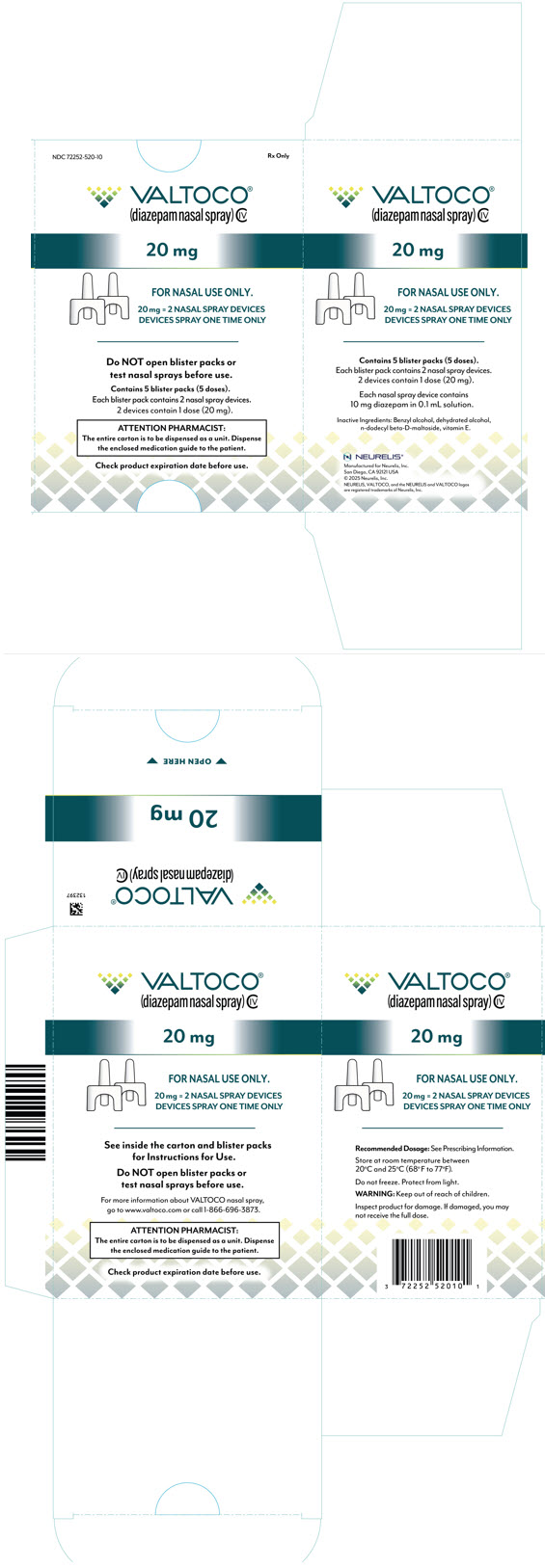 DRUG LABEL: Valtoco
NDC: 72252-505 | Form: SPRAY
Manufacturer: Neurelis, Inc
Category: prescription | Type: HUMAN PRESCRIPTION DRUG LABEL
Date: 20250923
DEA Schedule: CIV

ACTIVE INGREDIENTS: diazepam 5 mg/0.1 mL

HIGHLIGHTS OF PRESCRIBING INFORMATION

These highlights do not include all the information needed to use VALTOCO nasal spray safely and effectively. See full prescribing information for VALTOCO nasal spray.
VALTOCO® (diazepam nasal spray), CIV
Initial U.S. Approval: 1963

WARNING: RISKS FROM CONCOMITANT USE WITH OPIOIDS; ABUSE, MISUSE, AND ADDICTION; and DEPENDENCE AND WITHDRAWAL REACTIONS

See full prescribing information for complete boxed warning

- Concomitant use of benzodiazepines and opioids may result in profound sedation, respiratory depression, coma, and death. (5.1, 7.1)
- The use of benzodiazepines, including VALTOCO, exposes users to risks of abuse, misuse, and addiction, which can lead to overdose or death. Before prescribing VALTOCO and throughout treatment, assess each patient's risk for abuse, misuse, and addiction. (5.2)
- Although VALTOCO is indicated only for intermittent use (1, 2), if used more frequently than recommended, abrupt discontinuation or rapid dosage reduction of VALTOCO may precipitate acute withdrawal reactions, which can be life-threatening. For patients using VALTOCO more frequently than recommended, to reduce the risk of withdrawal reactions, use a gradual taper to discontinue VALTOCO. (5.3)

RECENT MAJOR CHANGES

Indications and Usage (1) | 04/2025
Dosage and Administration (2.2) | 04/2025

1 INDICATIONS AND USAGE

VALTOCO is a benzodiazepine indicated for the acute treatment of intermittent, stereotypic episodes of frequent seizure activity (i.e., seizure clusters, acute repetitive seizures) that are distinct from a patient's usual seizure pattern in patients with epilepsy 2 years of age and older. (1)

2 DOSAGE AND ADMINISTRATION

- Administer VALTOCO by the nasal route only. (2.3)
- Dosage is dependent on the patient's age and weight. (2.2)
- Initial Dose: VALTOCO 5 mg and 10 mg doses are administered as a single spray intranasally into one nostril. Administration of 15 mg and 20 mg doses requires two nasal spray devices, one spray into each nostril. (2.2)
- Second Dose: A second dose, when required, may be administered at least 4 hours after the initial dose. If administered, use a new blister pack. (2.2)
- Maximum Dosage and Treatment Frequency: Do not use more than 2 doses to treat a single episode. It is recommended that VALTOCO be used to treat no more than one episode every five days and no more than five episodes per month. (2.2)

3 DOSAGE FORMS AND STRENGTHS

Nasal spray: 5 mg, 7.5 mg, or 10 mg of diazepam in 0.1 mL. (3)

4 CONTRAINDICATIONS

- Hypersensitivity to diazepam. (4)
- Acute narrow-angle glaucoma. (4)

5 WARNINGS AND PRECAUTIONS

- CNS Depression: Monitor for central nervous system (CNS) depression. May cause an increased CNS-depressant effect when used with alcohol or other CNS depressants. (5.4, 7.2)
- Suicidal Behavior and Ideation: Monitor patients for suicidal ideation and behavior. (5.5)
- Glaucoma: VALTOCO can increase intraocular pressure in patients with glaucoma. VALTOCO may be used in patients with open-angle glaucoma only if they are receiving appropriate therapy. (4, 5.6)
- Neonatal Sedation and Withdrawal Syndrome: VALTOCO use during pregnancy can result in neonatal sedation and/or neonatal withdrawal. (5.7, 8.1)

6 ADVERSE REACTIONS

The most common adverse reactions (at least 4%) were somnolence, headache, and nasal discomfort. (6.1)

To report SUSPECTED ADVERSE REACTIONS, contact Neurelis, Inc. at 1-866-696-3873 or FDA at 1-800-FDA-1088 or www.fda.gov/medwatch.

7 DRUG INTERACTIONS

- CYP2C19 and CYP3A4 Inhibitors: Elimination of diazepam could be decreased with concurrent administration; therefore, adverse reactions with VALTOCO may be increased. (7.3)
- Inducers of CYP2C19 and CYP3A4 Inducers: Exposure of diazepam with concurrent administration may be decreased; therefore, efficacy with VALTOCO may be decreased. (7.3)

8 USE IN SPECIFIC POPULATIONS

Pregnancy: Based on animal data, may cause fetal harm. (8.1)

FULL PRESCRIBING INFORMATION

WARNING: RISKS FROM CONCOMITANT USE WITH OPIOIDS; ABUSE, MISUSE, AND ADDICTION; and DEPENDENCE AND WITHDRAWAL REACTIONS

- Concomitant use of benzodiazepines and opioids may result in profound sedation, respiratory depression, coma, and death. Reserve concomitant prescribing of these drugs for patients for whom alternative treatment options are inadequate. Limit dosages and durations to the minimum required. Follow patients for signs and symptoms of respiratory depression and sedation [see Warnings and Precautions (5.1) and Drug Interactions (7.1)].
- The use of benzodiazepines, including VALTOCO, exposes users to risks of abuse, misuse, and addiction, which can lead to overdose or death. Abuse and misuse of benzodiazepines commonly involve concomitant use of other medications, alcohol, and/or illicit substances, which is associated with an increased frequency of serious adverse outcomes. Before prescribing VALTOCO and throughout treatment, assess each patient's risk for abuse, misuse, and addiction [see Warnings and Precautions (5.2)].
- The continued use of benzodiazepines may lead to clinically significant physical dependence. The risks of dependence and withdrawal increase with longer treatment duration and higher daily dose. Although VALTOCO is indicated only for intermittent use [see Indications and Usage (1) and Dosage and Administration (2)], if used more frequently than recommended, abrupt discontinuation or rapid dosage reduction of VALTOCO may precipitate acute withdrawal reactions, which can be life-threatening. For patients using VALTOCO more frequently than recommended, to reduce the risk of withdrawal reactions, use a gradual taper to discontinue VALTOCO [see Warnings and Precautions (5.3)].

1 INDICATIONS AND USAGE

VALTOCO® is indicated for the acute treatment of intermittent, stereotypic episodes of frequent seizure activity (i.e., seizure clusters, acute repetitive seizures) that are distinct from a patient's usual seizure pattern in patients with epilepsy 2 years of age and older.

2 DOSAGE AND ADMINISTRATION

2.1 Instructions Prior to Dosing

Prior to treatment, healthcare professionals should instruct the individual administering VALTOCO on how to identify seizure clusters and use the product appropriately [see Dosage and Administration (2.3) and Patient Counseling Information (17)].

2.2 Dosing Information

The recommended dose of VALTOCO nasal spray is 0.2 mg/kg to 0.5 mg/kg, depending on the patient's age and weight. See Table 1 and Table 2 for specific recommendations.

Table 1: Recommended Dose Based on Age
Age (Years) | Recommended Dose
2 through 5 | 0.5 mg/kg
6 through 11 | 0.3 mg/kg
12 and older | 0.2 mg/kg

Table 2: Recommended Dosage and Administration for Adults and Pediatric Patients 2 Years of Age and Older
Dose Based on Age and Weight |  |  |  | Administration
2 to 5 Years of Age (0.5 mg/kg) | 6 to 11 Years of Age (0.3 mg/kg) | 12 Years of Age and Older (0.2 mg/kg) | Dose (mg) | Number of Nasal Spray Devices | Number of Sprays
Weight (kg)
6 to 11 | 10 to 18 | 14 to 27 | 5 | One 5 mg device | One spray in one nostril
12 to 22 | 19 to 37 | 28 to 50 | 10 | One 10 mg device | One spray in one nostril
23 to 33 | 38 to 55 | 51 to 75 | 15 | Two 7.5 mg devices | One spray in each nostril
 | 56 to 74 | 76 and up | 20 | Two 10 mg devices | One spray in each nostril

Second Dose (if needed): A second dose, when required, may be administered after at least 4 hours after the initial dose. If the second dose is to be administered, use a new blister pack of VALTOCO.

Maximum Dosage and Treatment Frequency: Do not use more than 2 doses of VALTOCO to treat a single episode.

Do not use VALTOCO to treat more than one episode every five days or more than five episodes per month.

2.3 Important Administration Instructions

VALTOCO is for intranasal use only.

No device assembly is required. VALTOCO nasal spray delivers its entire contents upon activation. Do not prime or attempt to use for more than one administration per device.

Patients and caregivers should be counseled to read carefully the "Instructions for Use" for complete directions on how to properly administer VALTOCO.

3 DOSAGE FORMS AND STRENGTHS

VALTOCO is available in 5 mg, 7.5 mg, and 10 mg strengths. Each VALTOCO nasal spray device contains 0.1 mL solution.

4 CONTRAINDICATIONS

VALTOCO nasal spray is contraindicated in patients with:

- Known hypersensitivity to diazepam
- Acute narrow angle glaucoma [see Warnings and Precautions (5.6)]

5 WARNINGS AND PRECAUTIONS

5.1 Risk of Concomitant Use with Opioids

Concomitant use of benzodiazepines, including VALTOCO, and opioids may result in profound sedation, respiratory depression, coma, and death [see Drug Interactions (7.1)]. Because of these risks, reserve concomitant prescribing of benzodiazepines and opioids for patients for whom alternative treatment options are inadequate.

Observational studies have demonstrated that concomitant use of opioid analgesics and benzodiazepines increases the risk of drug-related mortality compared to use of opioids alone. If a decision is made to prescribe VALTOCO concomitantly with opioids, prescribe the lowest effective dosages and minimum durations of concomitant use, and follow patients closely for signs and symptoms of respiratory depression and sedation. Advise both patients and caregivers about the risks of respiratory depression and sedation when VALTOCO is used with opioids.

5.2 Abuse, Misuse, and Addiction

The use of benzodiazepines, including VALTOCO, exposes users to the risks of abuse, misuse, and addiction, which can lead to overdose or death. Abuse and misuse of benzodiazepines often (but not always) involve the use of doses greater than the maximum recommended dosage and commonly involve concomitant use of other medications, alcohol, and/or illicit substances, which is associated with an increased frequency of serious adverse outcomes, including respiratory depression, overdose, or death [see Drug Abuse and Dependence (9.2)].

Before prescribing VALTOCO and throughout treatment, assess each patient's risk for abuse, misuse, and addiction. Use of VALTOCO, particularly in patients at elevated risk, necessitates counseling about the risks and proper use of VALTOCO along with monitoring for signs and symptoms of abuse, misuse, and addiction. Do not exceed the recommended dosing frequency; avoid or minimize concomitant use of CNS depressants and other substances associated with abuse, misuse, and addiction (e.g., opioid analgesics, stimulants); and advise patients on the proper disposal of unused drug. If a substance use disorder is suspected, evaluate the patient and institute (or refer them for) early treatment, as appropriate.

5.3 Dependence and Withdrawal Reactions After Use of VALTOCO More Frequently Than Recommended

For patients using VALTOCO more frequently than recommended, to reduce the risk of withdrawal reactions, use a gradual taper to discontinue VALTOCO (a patient-specific plan should be used to taper the dose).

Patients at an increased risk of withdrawal adverse reactions after benzodiazepine discontinuation or rapid dosage reduction include those who take higher dosages, and those who have had longer durations of use.

Acute Withdrawal Reactions

The continued use of benzodiazepines may lead to clinically significant physical dependence. Although VALTOCO is indicated only for intermittent use [see Indications and Usage (1) and Dosage and Administration (2)], if used more frequently than recommended, abrupt discontinuation or rapid dosage reduction of VALTOCO, or administration of flumazenil (a benzodiazepine antagonist) may precipitate acute withdrawal reactions, which can be life-threatening (e.g., seizures) [see Drug Abuse and Dependence (9.3)].

Protracted Withdrawal Syndrome

In some cases, benzodiazepine users have developed a protracted withdrawal syndrome with withdrawal symptoms lasting weeks to more than 12 months [see Drug Abuse and Dependence (9.3)].

5.4 CNS Depression

Benzodiazepines, including VALTOCO, produce CNS depression. Caution patients against engaging in hazardous activities requiring mental alertness (e.g., operating machinery, driving a motor vehicle, or riding a bicycle) until the effects of the drug, such as drowsiness, have subsided, and as their medical condition permits. Although VALTOCO is indicated for use solely on an intermittent basis, the potential for synergistic CNS-depressant effects when used simultaneously with alcohol or other CNS depressants must be considered by the prescriber and appropriate recommendations made to the patient and/or caregiver.

5.5 Suicidal Behavior and Ideation

Antiepileptic drugs (AEDs), including VALTOCO, increase the risk of suicidal thoughts or behavior in patients taking these drugs for any indication. Patients treated with any AED for any indication should be monitored for the emergence or worsening of depression, suicidal thoughts or behavior, and/or any unusual changes in mood or behavior.

Pooled analyses of 199 placebo-controlled clinical trials (mono- and adjunctive therapy) of 11 different AEDs showed that patients randomized to one of the AEDs had approximately twice the risk (adjusted Relative Risk 1.8, 95% CI:1.2, 2.7) of suicidal thinking or behavior compared to patients randomized to placebo. In these trials, which had a median treatment duration of 12 weeks, the estimated incidence rate of suicidal behavior or ideation among 27,863 AED-treated patients was 0.43%, compared to 0.24% among 16,029 placebo-treated patients, representing an increase of approximately one case of suicidal thinking or behavior for every 530 patients treated. There were four suicides in drug-treated patients in the trials and none in placebo-treated patients, but the number is too small to allow any conclusion about drug effect on suicide.

The increased risk of suicidal thoughts or behavior with AEDs was observed as early as one week after starting drug treatment with AEDs and persisted for the duration of treatment assessed. Because most trials included in the analysis did not extend beyond 24 weeks, the risk of suicidal thoughts or behavior beyond 24 weeks could not be assessed. The risk of suicidal thoughts or behavior was generally consistent among drugs in the data analyzed. The finding of increased risk with AEDs of varying mechanisms of action and across a range of indications suggests that the risk applies to all AEDs used for any indication. The risk did not vary substantially by age (5-100 years) in the clinical trials analyzed. Table 3 shows absolute and relative risk by indication for all evaluated AEDs.

Table 3: Risk by Indication for Antiepileptic Drugs in the Pooled Analysis
Indication | Placebo Patients with Events/1000 Patients | Drug Patients with Events per 1000 Patients | Relative Risk: Incidence of Drug Events in Drug Patients /Incidence in Placebo Patients | Risk Difference: Additional Drug Patients with Events per 1000 Patients
Epilepsy | 1.0 | 3.4 | 3.5 | 2.4
Psychiatric | 5.7 | 8.5 | 1.5 | 2.9
Other | 1.0 | 1.8 | 1.9 | 0.9
Total | 2.4 | 4.3 | 1.8 | 1.9

The relative risk for suicidal thoughts or behavior was higher in clinical trials for epilepsy than in clinical trials for psychiatric or other conditions, but the absolute risk differences were similar for the epilepsy and psychiatric indications.

Anyone considering prescribing VALTOCO or any other AED must balance the risk of suicidal thoughts or behaviors with the risk of untreated illness. Epilepsy and many other illnesses for which AEDs are prescribed are themselves associated with morbidity and mortality and an increased risk of suicidal thoughts and behavior. Should suicidal thoughts and behavior emerge during treatment, the prescriber needs to consider whether the emergence of these symptoms in any given patient may be related to the illness being treated.

5.6 Glaucoma

Benzodiazepines, including VALTOCO, can increase intraocular pressure in patients with glaucoma. VALTOCO may be used in patients with open-angle glaucoma only if they are receiving appropriate therapy. VALTOCO is contraindicated in patients with narrow-angle glaucoma.

5.7 Neonatal Sedation and Withdrawal Syndrome

Use of VALTOCO late in pregnancy can result in sedation (respiratory depression, lethargy, hypotonia) and/or withdrawal symptoms (hyperreflexia, irritability, restlessness, tremors, inconsolable crying, and feeding difficulties) in the neonate [see Use in Specific Populations (8.1)]. Monitor neonates exposed to VALTOCO during pregnancy or labor for signs of sedation and monitor neonates exposed to VALTOCO during pregnancy for signs of withdrawal; manage these neonates accordingly.

5.8 Risk of Serious Adverse Reactions in Infants due to Benzyl Alcohol Preservative

VALTOCO is not approved for use in neonates or infants. Serious and fatal adverse reactions including "gasping syndrome" can occur in neonates and low birth weight infants treated with benzyl alcohol-preserved drugs, including VALTOCO. The "gasping syndrome" is characterized by central nervous system depression, metabolic acidosis, and gasping respirations. The minimum amount of benzyl alcohol at which serious adverse reactions may occur is not known (VALTOCO contains 10.5 mg of benzyl alcohol per 0.1 mL) [see Use in Specific Populations (8.4)].

6 ADVERSE REACTIONS

The following serious adverse reactions are discussed elsewhere in the labeling:

- Risk of Concomitant Use with Opioids [see Warnings and Precautions (5.1)]
- Abuse, Misuse, and Addiction [see Warnings and Precautions (5.2)]
- Dependence and Withdrawal Reactions After Use of VALTOCO More Frequently Than Recommended [see Warnings and Precautions (5.3)]
- CNS depression [see Warnings and Precautions (5.4)]
- Suicidal Behavior and Ideation [see Warnings and Precautions (5.5)]
- Glaucoma [see Warnings and Precautions (5.6)]
- Neonatal Sedation and Withdrawal Syndrome [see Warnings and Precautions (5.7)]
- Risk of Serious Adverse Reactions in Infants due to Benzyl Alcohol Preservative [see Warnings and Precautions (5.8)].

6.1 Clinical Trials Experience

Because clinical studies are conducted under widely varying conditions, adverse reaction rates observed in the clinical studies of a drug cannot be directly compared to the rates in the clinical studies of another drug and may not reflect the rates observed in practice. The safety of VALTOCO is supported by clinical trials using diazepam rectal gel, as well as open-label, repeat-dose studies of VALTOCO in healthy subjects and epilepsy patients.

Diazepam Rectal Gel

In studies previously conducted with diazepam rectal gel, adverse event data were collected from double-blind, placebo-controlled studies and open-label studies. The majority of adverse events were mild to moderate in severity and transient in nature.

Two patients who received diazepam rectal gel died seven to 15 weeks following treatment; neither of these deaths was deemed related to diazepam rectal gel.

The most frequent adverse reactions (at least 4%) in the two double-blind, placebo-controlled studies were somnolence, headache, and diarrhea. Adverse events were usually mild or moderate in intensity.

Approximately 1.4% of the 573 patients who received diazepam rectal gel in clinical trials of epilepsy discontinued treatment because of an adverse event. The adverse reaction most frequently associated with discontinuation (occurring in three patients) was somnolence. Other adverse reactions most commonly associated with discontinuation and occurring in two patients were hypoventilation and rash. Adverse reactions associated with discontinuation occurring in one patient were asthenia, hyperkinesia, incoordination, vasodilatation, and urticaria.

In the two double-blind, placebo-controlled, parallel-group studies [see Clinical Studies (14)], the proportion of patients who discontinued treatment because of adverse events was 2% for the group treated with diazepam rectal gel, versus 2% for the placebo group. In the diazepam rectal gel group, one patient discontinued because of rash and one patient discontinued because of lethargy.

Table 4: Adverse Reactions That Occurred in Greater Than 1% Of Patients in Parallel-Group, Placebo-Controlled Trials with Diazepam Rectal Gel and More Common Than Placebo
Adverse Reaction | Diazepam Rectal Gel N=101 % | Placebo N=104 %
Somnolence | 23 | 8
Headache | 5 | 4
Diarrhea | 4 | <1
Ataxia | 3 | <1
Dizziness | 3 | 2
Euphoria | 3 | 0
Incoordination | 3 | 0
Rash | 3 | 0
Asthma | 2 | 0
Vasodilation | 2 | 0

VALTOCO (Diazepam Nasal Spray)

Clinical studies of patients with epilepsy 2 years of age and older were conducted to support the safety and tolerability of VALTOCO for the treatment of acute repetitive seizures. A total of 255 patients 2 years of age and older received VALTOCO, of whom 143 received VALTOCO for at least 1 year. Other than adverse reactions related to local nasal administration, the adverse reactions reported in these studies were similar to those seen in the efficacy trials of diazepam rectal gel.

The most common local adverse reactions that occurred in at least 1% of VALTOCO-treated patients were nasal discomfort (5%), dysgeusia (2%), epistaxis (2%), and rhinorrhea (1%).

Other Adverse Reactions

Diazepam rectal gel has previously been administered to 573 patients with epilepsy during all clinical trials, only some of which were placebo-controlled. All of the events listed below occurred in at least 1% of the 573 individuals exposed to diazepam rectal gel.

Body as a Whole: Asthenia

Cardiovascular: Hypotension, vasodilatation

Nervous: Agitation, confusion, convulsion, dysarthria, emotional lability, speech disorder, thinking abnormal, vertigo

Respiratory: Hiccup

The following infrequent adverse events have been reported previously with diazepam use: depression, slurred speech, syncope, changes in libido, urinary retention, bradycardia, cardiovascular collapse, nystagmus, urticaria, neutropenia, and jaundice.

Paradoxical reactions such as acute hyperexcited states, anxiety, hallucinations, increased muscle spasticity, insomnia, rage, sleep disturbances and stimulation have been reported with other diazepam products. If these events occur with the use of VALTOCO, the prescriber should consider discontinuation of use.

7 DRUG INTERACTIONS

7.1 Effect of Concomitant Use of Benzodiazepines and Opioids

The concomitant use of benzodiazepines and opioids increases the risk of respiratory depression because of actions at different receptor sites in the CNS that control respiration. Benzodiazepines interact at GABA-A sites, and opioids interact primarily at mu receptors. When benzodiazepines and opioids are combined, the potential for benzodiazepines to significantly worsen opioid-related respiratory depression exists [see Warnings and Precautions (5.1)]. Limit dosage and duration of concomitant use of benzodiazepines and opioids, and follow patients closely for respiratory depression and sedation.

7.2 CNS Depressants and Alcohol

Coadministration of other CNS depressants (e.g., valproate) or consumption of alcohol may potentiate the CNS-depressant effects of diazepam [see Warnings and Precautions (5.4)].

7.3 Effect of Other Drugs on VALTOCO Metabolism

Potential interactions may occur when diazepam is given concurrently with agents that affect CYP2C19 and CYP3A4 activity.

Inhibitors of CYP2C19 and CYP3A4

Inhibitors of CYP2C19 (e.g., cimetidine, quinidine, and tranylcypromine) and CYP3A4 (e.g., ketoconazole, troleandomycin, and clotrimazole) could decrease the rate of diazepam elimination; therefore, adverse reactions to VALTOCO may be increased.

Inducers of CYP2C19 and CYP3A4

Inducers of CYP2C19 (e.g., rifampin) and CYP3A4 (e.g., carbamazepine, phenytoin, dexamethasone, and phenobarbital) could increase the rate of diazepam elimination; therefore, efficacy of VALTOCO may be decreased.

7.4 Effect of VALTOCO on the Metabolism of Other Drugs

Diazepam is a substrate for CYP2C19 and CYP3A4; therefore, it is possible that VALTOCO may interfere with the metabolism of drugs which are substrates for CYP2C19 (e.g., omeprazole, propranolol, and imipramine) and CYP3A4 (e.g., cyclosporine, paclitaxel, theophylline, and warfarin) leading to a potential drug-drug interaction.

8 USE IN SPECIFIC POPULATIONS

8.1 Pregnancy

Pregnancy Exposure Registry

There is a pregnancy exposure registry that monitors pregnancy outcomes in women exposed to antiepileptic drugs (AEDs), such as VALTOCO, during pregnancy. Healthcare providers are encouraged to recommend that pregnant women who are taking VALTOCO during pregnancy enroll in the North American Antiepileptic Drug (NAAED) Pregnancy Registry by calling 1-888-233-2334 or visiting http://www.aedpregnancyregistry.org.

Risk Summary

Neonates born to mothers using benzodiazepines late in pregnancy have been reported to experience symptoms of sedation and/or neonatal withdrawal [see Warnings and Precautions (5.7) and Clinical Considerations]. Available data from published observational studies of pregnant women exposed to benzodiazepines do not report a clear association with benzodiazepines and major birth defects (see Human Data).

In animal studies, administration of diazepam during the organogenesis period of pregnancy resulted in increased incidences of fetal malformations at doses greater than those used clinically. Data for diazepam and other benzodiazepines suggest the possibility of increased neuronal cell death and long-term effects on neurobehavioral and immunological function based on findings in animals following prenatal or early postnatal exposure at clinically relevant doses (see Animal Data).

The background risk of major birth defects and miscarriage for the indicated population is unknown. All pregnancies have a background risk of birth defect, loss, or other adverse outcomes. In the U.S. general population, the estimated background risk of major birth defects and miscarriage in clinically recognized pregnancies is 2% to 4% and 15% to 20%, respectively.

Clinical Considerations

Fetal/Neonatal Adverse Reactions

Benzodiazepines cross the placenta and may produce respiratory depression, hypotonia, and sedation in neonates. Monitor neonates exposed to VALTOCO during pregnancy or labor for signs of sedation, respiratory depression, hypotonia, and feeding problems. Monitor neonates exposed to VALTOCO during pregnancy for signs of withdrawal. Manage these neonates accordingly [see Warnings and Precautions (5.7)].

Data

Human Data

Published data from observational studies on the use of benzodiazepines during pregnancy do not report a clear association with benzodiazepines and major birth defects.

Although early studies reported an increased risk of congenital malformations with diazepam and chlordiazepoxide, there was no consistent pattern noted. In addition, the majority of more recent case-control and cohort studies of benzodiazepine use during pregnancy, which were adjusted for confounding exposures to alcohol, tobacco, and other medications, have not confirmed these findings.

Animal Data

Diazepam has been shown to produce increased incidences of fetal malformations in mice and hamsters when given orally at single doses of 100 mg/kg or greater (approximately 13 times the maximum recommended human dose [MRHD = 0.6mg/kg/day] or greater on a mg/m^2 basis). Cleft palate and exencephaly are the most common and consistently reported malformations produced in these species by administration of high, maternally-toxic doses of diazepam during organogenesis.

In published animal studies, administration of benzodiazepines or other drugs that enhance GABAergic inhibition to neonatal rats has been reported to result in widespread apoptotic neurodegeneration in the developing brain at plasma concentrations relevant for seizure control in humans. The window of vulnerability to these changes in rats (postnatal days 0-14) includes a period of brain development that takes place during the third trimester of pregnancy in humans.

8.2 Lactation

Risk Summary

Diazepam is excreted in human milk.

There are reports of sedation, poor feeding, and poor weight gain in infants exposed to benzodiazepines through breast milk. There are no data to assess the effects of diazepam and/or its active metabolite(s) on milk production.

The developmental and health benefits of breastfeeding should be considered along with the mother's clinical need for VALTOCO nasal spray and any potential adverse effects on the breastfed infant from VALTOCO or from the underlying maternal condition.

Clinical Considerations

Infants exposed to VALTOCO through breast milk should be monitored for sedation, poor feeding and poor weight gain.

8.4 Pediatric Use

Safety and effectiveness of VALTOCO have been established in pediatric patients 2 years to 16 years of age. Use of VALTOCO in this age group is supported by evidence from adequate and well-controlled studies of diazepam rectal gel in adult and pediatric patients, adult bioavailability studies comparing VALTOCO with diazepam rectal gel, patient pharmacokinetic data, and open-label safety studies of VALTOCO including patients 2 years to 16 years of age [see Adverse Reactions (6.1), Clinical Pharmacology (12.3), and Clinical Studies (14)].

Safety and effectiveness of VALTOCO in pediatric patients below the age of 2 years have not been established.

VALTOCO is not approved for use in neonates or infants.

- Prolonged CNS depression has been observed in neonates treated with diazepam.
- Serious adverse reactions including fatal reactions and the "gasping syndrome" occurred in premature neonates and low-birth-weight infants in the neonatal intensive care unit who received drugs containing benzyl alcohol as a preservative. In these cases, benzyl alcohol dosages of 99 to 234 mg/kg/day produced high levels of benzyl alcohol and its metabolites in the blood and urine (blood levels of benzyl alcohol were 0.61 to 1.378 mmol/L). Additional adverse reactions included gradual neurological deterioration, seizures, intracranial hemorrhage, hematologic abnormalities, skin breakdown, hepatic and renal failure, hypotension, bradycardia, and cardiovascular collapse. Preterm, low-birth-weight infants may be more likely to develop these reactions because they may be less able to metabolize benzyl alcohol. The minimum amount of benzyl alcohol at which serious adverse reactions may occur is not known (VALTOCO contains 10.5 mg of benzyl alcohol per 0.1 mL) [see Warnings and Precautions (5.8)]

8.5 Geriatric Use

Clinical studies of VALTOCO did not include sufficient numbers of subjects aged 65 and over to determine whether they respond differently from younger subjects.

Therefore, in elderly patients, VALTOCO should be used with caution because of an increase in half-life with a corresponding decrease in the clearance of free diazepam [see Clinical Pharmacology (12.3)]. It is also recommended that the dosage be decreased to reduce the likelihood of ataxia or oversedation.

8.6 Compromised Respiratory Function

VALTOCO should be used with caution in patients with compromised respiratory function related to a concurrent disease process (e.g., asthma, pneumonia) or neurologic damage.

9 DRUG ABUSE AND DEPENDENCE

9.1 Controlled Substance

VALTOCO contains diazepam, a Schedule IV controlled substance.

9.2 Abuse

VALTOCO is a benzodiazepine and a CNS depressant with a potential for abuse and addiction. Abuse is the intentional, non-therapeutic use of a drug, even once, for its desirable psychological or physiological effects. Misuse is the intentional use, for therapeutic purposes, of a drug by an individual in a way other than prescribed by a health care provider or for whom it was not prescribed. Drug addiction is a cluster of behavioral, cognitive, and physiological phenomena that may include a strong desire to take the drug, difficulties in controlling drug use (e.g., continuing drug use despite harmful consequences, giving a higher priority to drug use than other activities and obligations), and possible tolerance or physical dependence. Even taking benzodiazepines as prescribed may put patients at risk for abuse and misuse of their medication. Abuse and misuse of benzodiazepines may lead to addiction.

Abuse and misuse of benzodiazepines often (but not always) involve the use of doses greater than the maximum recommended dosage and commonly involve concomitant use of other medications, alcohol, and/or illicit substances, which is associated with an increased frequency of serious adverse outcomes, including respiratory depression, overdose, or death. Benzodiazepines are often sought by individuals who abuse drugs and other substances, and by individuals with addictive disorders [see Warnings and Precautions (5.2)].

The following adverse reactions have occurred with benzodiazepine abuse and/or misuse: abdominal pain, amnesia, anorexia, anxiety, aggression, ataxia, blurred vision, confusion, depression, disinhibition, disorientation, dizziness, euphoria, impaired concentration and memory, indigestion, irritability, muscle pain, slurred speech, tremors, and vertigo.

The following severe adverse reactions have occurred with benzodiazepine abuse and/or misuse: delirium, paranoia, suicidal ideation and behavior, seizures, coma, breathing difficulty, and death. Death is more often associated with polysubstance use (especially benzodiazepines with other CNS depressants such as opioids and alcohol).

In the clinical studies with VALTOCO at recommended doses, abuse-related adverse events included euphoria, somnolence, sedation, anterograde amnesia, depression, anxiety, hallucinations, and restlessness.

9.3 Dependence

Physical Dependence After Use of VALTOCO More Frequently Than Recommended

VALTOCO may produce physical dependence if used more frequently than recommended. Physical dependence is a state that develops as a result of physiological adaptation in response to repeated drug use, manifested by withdrawal signs and symptoms after abrupt discontinuation or a significant dose reduction of a drug. Although VALTOCO is indicated only for intermittent use [see Indications and Usage (1) and Dosage and Administration (2)], if used more frequently than recommended, abrupt discontinuation or rapid dosage reduction or administration of flumazenil, a benzodiazepine antagonist, may precipitate acute withdrawal reactions, including seizures, which can be life-threatening. Patients at an increased risk of withdrawal adverse reactions after benzodiazepine discontinuation or rapid dosage reduction include those who take higher dosages (i.e., higher and/or more frequent doses) and those who have had longer durations of use [see Warnings and Precautions (5.3)]. For patients using VALTOCO more frequently than recommended, to reduce the risk of withdrawal reactions, use a gradual taper to discontinue VALTOCO [see Warnings and Precautions (5.3)].

Acute Withdrawal Signs and Symptoms

Acute withdrawal signs and symptoms associated with benzodiazepines have included abnormal involuntary movements, anxiety, blurred vision, depersonalization, depression, derealization, dizziness, fatigue, gastrointestinal adverse reactions (e.g., nausea, vomiting, diarrhea, weight loss, decreased appetite), headache, hyperacusis, hypertension, irritability, insomnia, memory impairment, muscle pain and stiffness, panic attacks, photophobia, restlessness, tachycardia, and tremor. More severe acute withdrawal signs and symptoms, including life-threatening reactions, have included catatonia, convulsions, delirium tremens, depression, hallucinations, mania, psychosis, seizures, and suicidality.

Protracted Withdrawal Syndrome

Protracted withdrawal syndrome associated with benzodiazepines is characterized by anxiety, cognitive impairment, depression, insomnia, formication, motor symptoms (e.g., weakness, tremor, muscle twitches), paresthesia, and tinnitus that persists beyond 4 to 6 weeks after initial benzodiazepine withdrawal. Protracted withdrawal symptoms may last weeks to more than 12 months. As a result, there may be difficulty in differentiating withdrawal symptoms from potential re-emergence or continuation of symptoms for which the benzodiazepine was being used.

Tolerance

Tolerance to VALTOCO may develop after use more frequently than recommended. Tolerance is a physiological state characterized by a reduced response to a drug after repeated administration (i.e., a higher dose of a drug is required to produce the same effect that was once obtained at a lower dose). Tolerance to the therapeutic effect of benzodiazepines may develop; however, little tolerance develops to the amnestic reactions and other cognitive impairments caused by benzodiazepines.

It is recommended that patients be treated with VALTOCO no more frequently than every five days and no more than five times per month.

VALTOCO is not recommended for chronic, daily use as an anticonvulsant. Chronic daily use of diazepam may increase the frequency and/or severity of tonic clonic seizures, requiring an increase in the dosage of standard anticonvulsant medication. In such cases, abrupt withdrawal of chronic diazepam may also be associated with a temporary increase in the frequency and/or severity of seizures.

10 OVERDOSAGE

Overdosage of benzodiazepines is characterized by central nervous system depression ranging from drowsiness to coma. In mild to moderate cases, symptoms can include drowsiness, confusion, dysarthria, lethargy, hypnotic state, diminished reflexes, ataxia, and hypotonia. Rarely, paradoxical or disinhibitory reactions (including agitation, irritability, impulsivity, violent behavior, confusion, restlessness, excitement, and talkativeness) may occur. In severe overdosage cases, patients may develop respiratory depression and coma. Overdosage of benzodiazepines in combination with other CNS depressants (including alcohol and opioids) may be fatal [see Warnings and Precautions (5.2)]. Markedly abnormal (lowered or elevated) blood pressure, heart rate, or respiratory rate raise the concern that additional drugs and/or alcohol are involved in the overdosage.

In managing benzodiazepine overdosage, employ general supportive measures, including intravenous fluids and airway maintenance. Flumazenil, a specific benzodiazepine receptor antagonist indicated for the complete or partial reversal of the sedative effects of benzodiazepines in the management of benzodiazepine overdosage, can lead to withdrawal and adverse reactions, including seizures, particularly in the context of mixed overdosage with drugs that increase seizure risk (e.g., tricyclic and tetracyclic antidepressants) and in patients with long-term benzodiazepine use and physical dependency. The risk of withdrawal seizures with flumazenil use may be increased in patients with epilepsy. Flumazenil is contraindicated in patients who have received a benzodiazepine for control of a potentially life-threatening condition (e.g., status epilepticus). If the decision is made to use flumazenil, it should be used as an adjunct to, not as a substitute for, supportive management of benzodiazepine overdosage. See the flumazenil injection Prescribing Information.

Consider contacting the Poison Help line (1-800-222-1222) or a medical toxicologist for additional overdosage management recommendations.

11 DESCRIPTION

Diazepam, the active ingredient of VALTOCO nasal spray, is a benzodiazepine anticonvulsant with the chemical name 7-chloro-1,3-dihydro-1-methyl-5-phenyl-2H-1,4-benzodiazepin-2-one; its molecular formula is C16H13ClN2O and its molecular weight is 284.7 g/mol. The structural formula is as follows:

The inactive ingredients in VALTOCO nasal spray include benzyl alcohol (10.5 mg per 0.1 mL), dehydrated alcohol, n-dodecyl beta-D-maltoside, and vitamin E. VALTOCO nasal spray is a clear pale amber liquid.

12 CLINICAL PHARMACOLOGY

12.1 Mechanism of Action

The exact mechanism of action for diazepam is not fully understood, but it is thought to involve potentiation of GABAergic neurotransmission resulting from binding at the benzodiazepine site of the GABAA receptor.

12.2 Pharmacodynamics

The effects of diazepam on the CNS are dependent on the dose administered, the route of administration, and the presence or absence of other medications.

12.3 Pharmacokinetics

Pharmacokinetic information for VALTOCO following nasal administration was obtained from studies conducted in healthy adult subjects, as well as adult and pediatric patients with epilepsy 2 years of age and older.

Absorption

In a pharmacokinetic study in healthy adult subjects, the highest plasma diazepam concentrations after nasal administration of VALTOCO was reached in 1.5 hours. The estimated volume of distribution of diazepam at steady-state is 0.8 to 1.0 L/kg. The absolute bioavailability of VALTOCO relative to intravenous diazepam was 97%. The mean elimination half-life of diazepam following administration of a 10 mg dose of VALTOCO was found to be about 49.2 hours. In another pharmacokinetic study in healthy adult subjects, diazepam plasma exposures (Cmax and AUC) increased approximately proportional to dose from 5 mg to 20 mg.

In a relative bioavailability study in healthy adult subjects, diazepam exposure (Cmax and AUCs) was evaluated following administration of 15 and 20 mg of VALTOCO nasal spray and diazepam rectal gel. The diazepam PK parameters were 2 to 4-fold less variable for VALTOCO and within the range of those seen with diazepam rectal gel.

In a pharmacokinetic study in patients with epilepsy, pharmacokinetic parameters were similar between seizure versus non-seizure states.

Distribution

Both diazepam and its major active metabolite desmethyldiazepam bind extensively to plasma proteins (95-98%).

Metabolism and Elimination

In vitro studies using human liver preparations suggest that CYP2C19 and CYP3A4 are the principal isozymes involved in the initial oxidative metabolism of diazepam. It has been reported in the literature that diazepam is extensively metabolized to one major active metabolite, desmethyldiazepam, and two minor active metabolites, 3- hydroxydiazepam (temazepam) and 3-hydroxy-N-diazepam (oxazepam), in plasma. At therapeutic doses, desmethyldiazepam is found in plasma at concentrations equivalent to those of diazepam while oxazepam and temazepam are not usually detectable. The metabolism of diazepam is primarily hepatic and involves demethylation (involving primarily CYP2C19 and CYP3A4) and 3-hydroxylation (involving primarily CYP3A4), followed by glucuronidation. The marked inter-individual variability in the clearance of diazepam reported in the literature is probably attributable to variability of CYP2C19 (which is known to exhibit genetic polymorphism; about 3-5% of Caucasians have little or no activity and are "poor metabolizers") and CYP3A4. No inhibition was demonstrated in the presence of inhibitors selective for CYP2A6, CYP2C9, CYP2D6, CYP2E1, or CYP1A2, indicating that these enzymes are not significantly involved in metabolism of diazepam.

Specific Populations

Geriatric Patients

A study of single dose IV administration of diazepam (0.1 mg/kg) indicates that the elimination half-life of diazepam increases linearly with age, ranging from about 15 hours at 18 years (healthy young adults) to about 100 hours at 95 years (healthy elderly) with a corresponding decrease in clearance of free diazepam [see Use in Specific Populations (8.5)].

Pediatric Patients

Literature review indicates that following IV administration (0.33 mg/kg), diazepam has a half-life in pediatric patients 6 to 12 years of age of approximately 15-21 hours. Based on simulation studies, in pediatric patients 2 to 5 years of age, median maximum plasma concentration (Cmax) and median area under the plasma concentration curve (AUC0-t) of diazepam following a single administration of VALTOCO are approximately 2-times greater than in adults. In pediatric patients 6 to 11 years of age, median Cmax and median AUC0-t of diazepam following a single administration of VALTOCO are approximately 1.4-times greater than in adults.

Patients with Renal Impairment

The pharmacokinetics of diazepam have not been studied in subjects with renal impairment.

Patients with Hepatic Impairment

No pharmacokinetic studies were conducted with VALTOCO in subjects with hepatic impairment. Literature review indicates that following administration of 0.1 to 0.15 mg/kg of diazepam intravenously, the half-life of diazepam was prolonged by two to five-fold in subjects with alcoholic cirrhosis (n=24) compared to age-matched control subjects (n=37) with a corresponding decrease in clearance by half. However, the exact degree of hepatic impairment in these subjects was not characterized in this literature.

Effect of Gender, Race, and Cigarette Smoking

No targeted pharmacokinetic studies have been conducted to evaluate the effect of gender, race, and cigarette smoking on the pharmacokinetics of diazepam. However, covariate analysis of a population of treated patients following administration of diazepam rectal gel, indicated that neither gender nor cigarette smoking had any effect on the pharmacokinetics of diazepam.

13 NONCLINICAL TOXICOLOGY

13.1 Carcinogenesis, Mutagenesis, Impairment of Fertility

Carcinogenesis

The carcinogenic potential of diazepam delivered by the intranasal route of administration has not been evaluated. In studies in which mice and rats were administered diazepam orally in the diet at a dose of 75 mg/kg/day (approximately 10 and 20 times, respectively, the maximum recommended human dose [MRHD=0.6 mg/kg/day] on a mg/m^2 basis) for 80 and 104 weeks, respectively, an increased incidence of liver tumors was observed in males of both species.

Mutagenesis

The data currently available are inadequate to determine the mutagenic potential of diazepam.

Impairment of Fertility

Reproduction studies with orally administered diazepam in rats showed decreases in the number of pregnancies and in the number of surviving offspring following administration of an oral dose of 100 mg/kg/day (approximately 27 times the MRHD on a mg/m^2 basis) prior to and during mating and throughout gestation and lactation. No adverse effects on fertility or offspring viability were noted at a dose of 80 mg/kg/day (approximately 22 times the MRHD on a mg/m^2 basis).

14 CLINICAL STUDIES

The efficacy of VALTOCO is based on the relative bioavailability of VALTOCO nasal spray compared to diazepam rectal gel in healthy adults [see Clinical Pharmacology (12.3)].

The effectiveness of diazepam rectal gel has been established in two adequate and well-controlled clinical studies in children and adults exhibiting seizure patterns.

A randomized, double-blind study compared sequential doses of diazepam rectal gel and placebo in 91 patients (47 children, 44 adults) exhibiting the appropriate seizure profile. The first dose was given at the onset of an identified episode. Children were dosed again four hours after the first dose and were observed for a total of 12 hours. Adults were dosed at four and 12 hours after the first dose and were observed for a total of 24 hours. Primary outcomes for this study were seizure frequency during the period of observation and a global assessment that took into account the severity and nature of the seizures as well as their frequency.

The median seizure frequency for the diazepam rectal gel treated group was zero seizures per hour, compared to a median seizure frequency of 0.3 seizures per hour for the placebo group, a difference that was statistically significant (p < 0.0001). All three categories of the global assessment (seizure frequency, seizure severity, and "overall") were also found to be statistically significant in favor of diazepam rectal gel (p < 0.0001). The following histogram displays the results for the "overall" category of the global assessment.

Figure 1: Caregiver Overall Global Assessment of the Efficacy of Diazepam Rectal Gel

Patients treated with diazepam rectal gel experienced prolonged time-to-next-seizure compared to placebo (p = 0.0002) as shown in the following graph.

Figure 2: Kaplan-Meier Survival Analysis of Time-to-Next-Seizure - First Study

In addition, 62% of patients treated with diazepam rectal gel were seizure-free during the observation period compared to 20% of placebo patients.

Analysis of response by gender and age revealed no substantial differences between treatment in either of these subgroups. Analysis of response by race was considered unreliable, due to the small percentage of non-Caucasians.

A second double-blind study compared single doses of diazepam rectal gel and placebo in 114 patients (53 children, 61 adults). The dose was given at the onset of the identified episode and patients were observed for a total of 12 hours. The primary outcome in this study was seizure frequency. The median seizure frequency for the diazepam rectal gel-treated group was zero seizures per 12 hours, compared to a median seizure frequency of 2.0 seizures per 12 hours for the placebo group, a difference that was statistically significant (p < 0.03). Patients treated with diazepam rectal gel experienced prolonged time-to-next-seizure compared to placebo (p = 0.0072) as shown in Figure 3.

Figure 3: Kaplan-Meier Survival Analysis of Time-to-Next-Seizure - Second Study

In addition, 55% of patients treated with diazepam rectal gel were seizure-free during the observation period compared to 34% of patients receiving placebo. Overall, caregivers judged diazepam rectal gel to be more effective than placebo (p = 0.018), based on a 10-centimeter visual analog scale. In addition, investigators also evaluated the effectiveness of diazepam rectal gel and judged diazepam rectal gel to be more effective than placebo (p < 0.001).

An analysis of response by gender revealed a statistically significant difference between treatments in females but not in males in this study, and the difference between the 2 genders in response to the treatments reached borderline statistical significance. Analysis of response by race was considered unreliable, due to the small percentage of non-Caucasians.

16 HOW SUPPLIED/STORAGE AND HANDLING

16.1 How Supplied

VALTOCO is available in 5 mg, 7.5 mg, and 10 mg strengths. VALTOCO is supplied and packaged in doses of 5 mg, 10 mg, 15 mg, or 20 mg (see Table 5).

Table 5: Available Packaging Configurations
Description | Contents | NDC
Each Carton Contains 2 Doses
5 mg carton | 2 individual blister packs, each containing one 5 mg nasal spray device | 72252-505-02
10 mg carton | 2 individual blister packs, each containing one 10 mg nasal spray device | 72252-510-02
15 mg carton | 2 individual blister packs, each containing two 7.5 mg nasal spray devices | 72252-515-04
20 mg carton | 2 individual blister packs, each containing two 10 mg nasal spray devices | 72252-520-04
Each Carton Contains 5 Doses
5 mg carton | 5 individual blister packs, each containing one 5 mg nasal spray device | 72252-505-05
10 mg carton | 5 individual blister packs, each containing one 10 mg nasal spray device | 72252-510-05
15 mg carton | 5 individual blister packs, each containing two 7.5 mg nasal spray devices | 72252-515-10
20 mg carton | 5 individual blister packs, each containing two 10 mg nasal spray devices | 72252-520-10

16.2 Storage and Handling

Do not open individual blister packs or test nasal spray devices before use.

Each single-dose nasal spray device sprays one (1) time and cannot be re-used.

Do not use if the nasal spray unit appears damaged.

Store VALTOCO at 20°C to 25°C (68°F to 77°F); excursions permitted from 15°C to 30°C (59°F to 86°F) [see USP Controlled Room Temperature]. Do not freeze. Protect from light.

17 PATIENT COUNSELING INFORMATION

Advise the patient and/or caregiver to read the FDA-approved patient labeling (Medication Guide and Instructions for Use).

Concomitant use with Opioids

Concomitant use of benzodiazepines, including VALTOCO, and opioids may result in profound sedation, respiratory depression, coma, and death. Do not use such drugs concomitantly unless supervised by a health care provider [see Warnings and Precautions (5.1)].

Abuse, Misuse, and Addiction

Inform patients that the use of VALTOCO more frequently than recommended, even at recommended dosages, exposes users to risks of abuse, misuse, and addiction, which can lead to overdose and death, especially when used in combination with other medications (e.g., opioid analgesics), alcohol, and/or illicit substances. Inform patients about the signs and symptoms of benzodiazepine abuse, misuse, and addiction; to seek medical help if they develop these signs and/or symptoms; and on the proper disposal of unused drug [see Warnings and Precautions (5.2) and Drug Abuse and Dependence (9.2)].

Withdrawal Reactions

Inform patients that use of VALTOCO more frequently than recommended may lead to clinically significant physical dependence and that abrupt discontinuation or rapid dosage reduction of VALTOCO may precipitate acute withdrawal reactions, which can be life-threatening. Inform patients that in some cases, patients taking benzodiazepines have developed a protracted withdrawal syndrome with withdrawal symptoms lasting weeks to more than 12 months [see Warnings and Precautions (5.3) and Drug Abuse and Dependence (9.3)].

Important Treatment Instructions

Instruct patients and caregivers on what is and is not an intermittent and stereotypic episode of increased seizure activity (i.e., seizure cluster) that is appropriate for treatment, and the timing of administration in relation to the onset of the episode.

Instruct patients and caregivers on what to observe following administration, and what would constitute an outcome requiring immediate medical attention.

Instruct patients and caregivers not to administer a second dose of VALTOCO if they are concerned by the patient's breathing, the patient requires emergency rescue treatment with assisted breathing or intubation, or there is excessive sedation [see Use in Specific Populations (8.6)].

Advise patients and caregivers on how frequently they can treat successive seizure cluster episodes over time.

Pregnancy

Advise pregnant females that the use of VALTOCO late in pregnancy can result in sedation (respiratory depression, lethargy, hypotonia) and/or withdrawal symptoms (hyperreflexia, irritability, restlessness, tremors, inconsolable crying, and feeding difficulties) in newborns [see Warnings and Precautions (5.7) and Use in Specific Populations (8.1)]. Instruct patients to inform their healthcare provider if they are pregnant. Encourage patients to enroll in the North American Antiepileptic Drug (NAAED) Pregnancy Registry if they become pregnant while taking VALTOCO. The registry is collecting information about the safety of antiepileptic drugs during pregnancy [see Use in Specific Populations (8.1)].

Lactation

Counsel patients that diazepam, the active ingredient in VALTOCO, is excreted in breast milk. Instruct patients to inform their healthcare provider if they are breastfeeding or intend to breastfeed. Instruct breastfeeding patients who take VALTOCO to monitor their infants for excessive sedation, poor feeding and poor weight gain, and to seek medical attention if they notice these signs [see Use in Specific Populations (8.2)].

NEURELIS, VALTOCO and the NEURELIS and VALTOCO logos are registered trademarks of Neurelis, Inc.

Distributed by: Neurelis, Inc. San Diego, CA 92121 USA

© 2025 Neurelis, Inc. All rights reserved.

Neurelis Rev. 06/2025 US-PRC-25-00099-v2

MEDICATION GUIDE
VALTOCO® (val-toe-koe)
(diazepam nasal spray), CIV

What is the most important information I should know about VALTOCO?

- VALTOCO is a benzodiazepine medicine. Taking benzodiazepines with opioid medicines, alcohol, or other central nervous system (CNS) depressants (including street drugs) can cause severe drowsiness, breathing problems (respiratory depression), coma, and death. Get emergency medical help right away if any of the following happens:
  - shallow or slowed breathing
  - breathing stops (which may lead to the heart stopping)
  - excessive sleepiness (sedation)
  Do not drive or operate heavy machinery until you know how taking VALTOCO with opioids affects you.

- Risk of abuse, misuse, and addiction. There is a risk for abuse, misuse, and addiction with benzodiazepines, including VALTOCO, which can lead to overdose and serious side effects including coma and death.
  - Serious side effects including coma and death have happened in people who have abused or misused benzodiazepines, including diazepam (the active ingredient in VALTOCO). These serious side effects may also include delirium, paranoia, suicidal thoughts or actions, seizures, and difficulty breathing. Call your healthcare provider or go to the nearest hospital emergency room right away if you get any of these serious side effects.
  - You can develop an addiction even if you use VALTOCO as prescribed by your healthcare provider.
  - Use VALTOCO exactly as your healthcare provider prescribed.
  - Do not share your VALTOCO with other people.
  - Keep VALTOCO in a safe place and away from children.

- Physical dependence and withdrawal reactions. Benzodiazepines, including VALTOCO, can cause physical dependence and withdrawal reactions, especially if you use VALTOCO daily. VALTOCO is not intended for daily use.
  - Do not suddenly stop using VALTOCO without talking to your healthcare provider. Stopping VALTOCO suddenly can cause serious and life-threatening side effects, including, unusual movements, responses, or expressions, seizures, sudden and severe mental or nervous system changes, depression, seeing or hearing things that others do not see or hear, an extreme increase in activity or talking, losing touch with reality, and suicidal thoughts or actions. Call your healthcare provider or go to the nearest hospital emergency room right away if you get any of these symptoms.
  - Some people who suddenly stop benzodiazepines have symptoms that can last for several weeks to more than 12 months, including, anxiety, trouble remembering, learning, or concentrating, depression, problems sleeping, feeling like insects are crawling under your skin, weakness, shaking, muscle twitching, burning or prickling feeling in your hands, arms, legs or feet, and ringing in your ears.
  - Physical dependence is not the same as drug addiction. Your healthcare provider can tell you more about the differences between physical dependence and drug addiction.
  - Do not use more VALTOCO than prescribed or use VALTOCO more often than prescribed.

- VALTOCO can make you sleepy or dizzy and can slow your thinking and motor skills.
  - Do not drive, operate heavy machinery, or do other dangerous activities until you know how VALTOCO affects you.
  - Do not drink alcohol or take other drugs that may make you sleepy or dizzy while using VALTOCO without first talking to your healthcare provider. When taken with alcohol or drugs that cause sleepiness or dizziness, VALTOCO may make your sleepiness or dizziness worse.

- Like other antiepileptic medicines, VALTOCO may cause suicidal thoughts or actions in a small number of people, about 1 in 500. Call your healthcare provider right away if you have any of these symptoms, especially if they are new, worse, or worry you:

- thoughts about suicide or dying
- feeling agitated or restless
- acting aggressive, being angry, or violent
- attempts to commit suicide
- panic attacks
- acting on dangerous impulses

- trouble sleeping (insomnia)
- an extreme increase in activity and talking (mania)
- new or worse anxiety
- new or worse irritability
- other unusual changes in behavior or mood
- new or worse depression

How can I watch for early symptoms of suicidal thoughts or actions?

- Pay attention to any changes, especially sudden changes in mood, behaviors, thoughts, or feelings.
- Keep all follow-up visits with your healthcare provider as scheduled.

Call your healthcare provider between visits as needed, especially if you are worried about symptoms. Suicidal thoughts or actions can be caused by things other than medicines. If you have suicidal thoughts or actions, your healthcare provider may check for other causes.

What is VALTOCO?

- VALTOCO is a prescription medicine used for short-term treatment of seizure clusters (also known as "acute repetitive seizures") that are different from a person's normal seizure pattern in people 2 years of age and older.
- VALTOCO is a federally controlled substance (C-IV) because it contains diazepam that can be abused or lead to dependence. Keep VALTOCO in a safe place to prevent misuse and abuse. Selling or giving away VALTOCO may harm others and is against the law. Tell your healthcare provider if you have abused or been dependent on alcohol, prescription drugs, or street drugs.
- It is not known if VALTOCO is safe and effective in children under 2 years of age.

Do not use VALTOCO if you:

- are allergic to diazepam or any of the ingredients in VALTOCO. See the end of this Medication Guide for a complete list of ingredients in VALTOCO.
- have an eye problem called acute narrow angle glaucoma.

Before using VALTOCO, tell your healthcare provider about all of your medical conditions, including if you:

- have asthma, emphysema, bronchitis, chronic obstructive pulmonary disease, or other breathing problems.
- have a history of alcohol or drug abuse.
- have a history of depression, mood problems or suicidal thoughts or behaviors.
- have liver or kidney problems.
- are pregnant or plan to become pregnant.
  - Taking VALTOCO late in pregnancy may cause your baby to have symptoms of sedation (breathing problems, sluggishness, low muscle tone) and/or withdrawal symptoms (jitteriness, irritability, restlessness, shaking, excessive crying, feeding problems).
  - Tell your healthcare provider right away if you become pregnant or think you are pregnant during treatment with VALTOCO.
  - If you become pregnant while using VALTOCO, talk to your healthcare provider about registering with the North American Antiepileptic Drug (NAAED) Pregnancy Registry. You can register by calling 1-888-233-2334. For more information about the registry, go to http://www.aedpregnancyregistry.org. The purpose of this registry is to collect information about the safety of antiepileptic drugs during pregnancy.
- are breastfeeding or plan to breastfeed. VALTOCO passes into your breast milk and may harm your baby.
  - Breastfeeding during treatment with VALTOCO may cause your baby to have sleepiness, feeding problems, and decreased weight gain.
  - Talk to your healthcare provider about the best way to feed your baby if you use VALTOCO.

Tell your healthcare provider about all the medicines you take, including prescription and over-the-counter medicines, vitamins, and herbal supplements. Using VALTOCO with certain other medicines can cause side effects or affect how well VALTOCO or the other medicines work. Do not start or stop other medicines without talking to your healthcare provider.

How should I use VALTOCO?

- Read the Instructions for Use that comes with this Medication Guide for detailed information about the right way to use VALTOCO.
- Use VALTOCO exactly as prescribed by your healthcare provider.
- Your healthcare provider will tell you:
  - what seizure clusters are
  - exactly how much VALTOCO to give
  - when to give VALTOCO
  - how to give VALTOCO
  - what to do after you give VALTOCO if the seizures do not stop or there is a change in breathing, behavior, or condition that worries you
- You should carry VALTOCO with you in case you need it to control your seizure clusters.
- Family members, care providers, and other people who may have to give VALTOCO should know where you keep your VALTOCO and how to give VALTOCO before a seizure cluster happens.
- VALTOCO is given in the nose (nasal) only.
- Do not test or prime the nasal spray before use.
- Each VALTOCO only sprays 1 time and cannot be reused.
- Each dose of VALTOCO is provided in an individual pack. Use all of the medicine in 1 pack for a complete dose.

What should I do after I give VALTOCO?

- Stay with the person after you give VALTOCO and watch them closely.
- Make a note of the time VALTOCO was given.
- Call for emergency help if any of the following happen:
  - seizure cluster behavior is different than other seizure clusters the person has had.
  - you are alarmed by how often the seizures happen, by how severe the seizure is, by how long the seizure lasts, or by the color or breathing of the person.
- Throw away (discard) the used VALTOCO.

If needed, a second dose may be given at least 4 hours after the first dose, using a new pack of VALTOCO. Do not give more than 2 doses of VALTOCO to treat a seizure cluster.
A second dose should not be given if there is concern about the person's breathing, they need help with their breathing, or have extreme drowsiness.

Do not use VALTOCO for more than 1 seizure cluster episode every 5 days. Do not use VALTOCO for more than 5 seizure cluster episodes in 1 month.

What should I avoid while using VALTOCO?
See "What is the most important information I should know about VALTOCO?"
What are the possible side effects of VALTOCO?
VALTOCO may cause serious side effects, including:

- See "What is the most important information I should know about VALTOCO?"
- Increase in eye pressure in people with open-angle glaucoma. See "Do not use VALTOCO if you:"

The most common side effects of VALTOCO include:

- feeling sleepy or drowsy

- headache

- nose discomfort

These are not all of the possible side effects of VALTOCO. Call your doctor for medical advice about side effects.
You may report side effects to FDA at 1-800-FDA-1088.

How should I store VALTOCO?

- Store VALTOCO at room temperature between 68°F to 77°F (20°C to 25°C).
- Do not freeze VALTOCO.
- Keep VALTOCO in its blister pack until ready to use. Protect it from light.
- Keep VALTOCO and all medicines out of the reach of children.

General information about the safe and effective use of VALTOCO.

Medicines are sometimes prescribed for purposes other than those listed in a Medication Guide. Do not use VALTOCO for a condition for which it was not prescribed. Do not give VALTOCO to other people, even if they have the same symptoms that you have. It may harm them. You can ask your pharmacist or healthcare provider for information about VALTOCO that is written for health professionals.

What are the ingredients in VALTOCO?

Active ingredient: diazepam

Inactive ingredients: benzyl alcohol, dehydrated alcohol, n-dodecyl beta-D-maltoside, and vitamin E.

Distributed by Neurelis, Inc., San Diego, CA 92121 USA. NEURELIS and VALTOCO and the NEURELIS and VALTOCO logos are registered trademarks of Neurelis, Inc.
For more information, go to www.valtoco.com or call 1-866-696-3873.

This Medication Guide has been approved by the U.S. Food and Drug Administration.

Revised: 04/2025 US-PRC-25-00100-v1

INSTRUCTIONS FOR USE

For 5 mg and 10 mg Doses

VALTOCO®
(diazepam nasal spray) CIV

You, your family members, caregivers, and others who may need to give VALTOCO should read these Instructions for Use before using it. Talk to your healthcare provider if you, your caregiver, or others who may need to give VALTOCO have any questions about the use of VALTOCO.

Important: For Nasal Use Only.

Do not test or prime the nasal spray device. Each device sprays one time only.
Do not use past the expiration date printed on box and blister pack.
Do not open blister pack until ready to use.

Each blister pack contains
1 nasal spray device.
1 dose = 1 nasal spray device.

To give VALTOCO nasal spray:

 | Step 1: | Open the blister pack by peeling back the corner tab with the arrow. Remove the nasal spray device from the blister pack.
 | Step 2: | Hold the nasal spray device with your thumb on the bottom of the plunger and your first and middle fingers on either side of the nozzle. Do not press the plunger yet. If you press the plunger now, you will lose the medicine.
 | Step 3: | Insert the tip of the nozzle into 1 nostril until your fingers, on either side of the nozzle, are against the bottom of the nose.
 | Step 4: | Press the bottom of the plunger firmly with your thumb to give VALTOCO. The person does not need to breathe deeply when VALTOCO is given. Remove the nasal spray device from the nose after giving VALTOCO.

After giving VALTOCO nasal spray:

Throw away (discard) the nasal spray device and the blister pack after use.

Call for emergency help if any of the following happen:

- Seizure behavior in the person is different from that of other episodes.
- You are alarmed by how often the seizures happen, by how severe the seizure is, by how long the seizure lasts, or by the color or breathing of the person.

Make a note of the time VALTOCO was given and continue to watch the person closely.

Time of first VALTOCO dose:______________ Time of second VALTOCO dose (if given): ______________________

The healthcare provider may prescribe another dose of VALTOCO to be given at least 4 hours after the first dose. If a second dose is needed, repeat Steps 1 through 4 with a new blister pack of VALTOCO.

For more information about VALTOCO, visit www.valtoco.com or call 1-866-696-3873. Report side effects of prescription drugs to the FDA by visiting www.fda.gov/medwatch or by calling 1-800-FDA-1088.

These Instructions for Use have been approved by the U.S. Food and Drug Administration. Issued: 02/2022

© Neurelis, Inc. 2022. NEURELIS, VALTOCO, and the NEURELIS and VALTOCO logos are trademarks or registered trademarks of Neurelis, Inc. US-PRC-22-00029 02/2022

INSTRUCTIONS FOR USE

For 15 mg and 20 mg Doses

VALTOCO®
(diazepam nasal spray) CIV

You, your family members, caregivers, and others who may need to give VALTOCO should read these Instructions for Use before using it. Talk to your healthcare provider if you, your caregiver, or others who may need to give VALTOCO have any questions about the use of VALTOCO.

Important: For Nasal Use Only.

Do not test or prime the nasal spray devices. Each device sprays one time only.
Do not use past the expiration date printed on box and blister pack.
Do not open blister pack until ready to use.

Each blister pack contains
2 nasal spray devices.
1 dose = 2 nasal spray devices.

To give VALTOCO nasal spray:

 | Step 1: | Open the blister pack by peeling back the corner tab with the arrow. Remove the first nasal spray device from the blister pack.
 | Step 2: | Hold the nasal spray device with your thumb on the bottom of the plunger and your first and middle fingers on either side of the nozzle. Do not press the plunger yet. If you press the plunger now, you will lose the medicine.
 | Step 3: | Insert the tip of the nozzle into 1 nostril until your fingers, on either side of the nozzle, are against the bottom of the nose.
 | Step 4: | Press the bottom of the plunger firmly with your thumb to give VALTOCO. The person does not need to breathe deeply when VALTOCO is given. Remove the nasal spray device from the nose after giving VALTOCO.
 | Step 5: | You have not given the full dose of VALTOCO yet. Remove the second nasal spray device from the blister pack. Repeat Steps 2 through 4, using the second nasal spray device in the other nostril to give the full dose of VALTOCO.

After giving VALTOCO nasal spray:

Throw away (discard) both nasal spray devices and the blister pack after use.

Call for emergency help if any of the following happen:

- Seizure behavior in the person is different from that of other episodes.
- You are alarmed by how often the seizures happen, by how severe the seizure is, by how long the seizure lasts, or by the color or breathing of the person.

Make a note of the time VALTOCO was given and continue to watch the person closely.

Time of first VALTOCO dose (first dose equals 1 spray in each nostril):________________/________________
Time of second VALTOCO dose (if given, second dose equals 1 spray in each nostril):________________/________________

The healthcare provider may prescribe another dose of VALTOCO to be given at least 4 hours after the first dose. If a second dose is needed, repeat Steps 1 through 5 with a new blister pack of VALTOCO.

For more information about VALTOCO, visit www.valtoco.com or call 1-866-696-3873. Report side effects of prescription drugs to the FDA by visiting www.fda.gov/medwatch or by calling 1-800-FDA-1088.

These Instructions for Use have been approved by the U.S. Food and Drug Administration. Issued: 02/2022

© Neurelis, Inc. 2022. NEURELIS, VALTOCO, and the NEURELIS and VALTOCO logos are trademarks or registered trademarks of Neurelis, Inc. US-PRC-22-00029 02/2022

PRINCIPAL DISPLAY PANEL - 5 mg Device Blister Pack Carton - 2 Doses

NDC 72252-505-02
Rx Only

VALTOCO®
(diazepam nasal spray) CIV

5 mg

FOR NASAL USE ONLY.

5 mg = 1 NASAL SPRAY DEVICE
DEVICE SPRAYS ONE TIME ONLY

Do NOT open blister packs or
test nasal sprays before use.

This box contains 2 blister packs.
Each blister pack contains 1 nasal spray device.
1 device contains 1 dose (5 mg)

ATTENTION PHARMACIST:
The entire carton is to be dispensed as a unit. Dispense
the enclosed medication guide to the patient.

Check product expiration date before use.

PRINCIPAL DISPLAY PANEL - 5 mg Device Blister Pack Carton - 5 Doses

NDC 72252-505-05
Rx Only

VALTOCO®
(diazepam nasal spray) CIV

5 mg

FOR NASAL USE ONLY.

5 mg = 1 NASAL SPRAY DEVICE
DEVICE SPRAYS ONE TIME ONLY

Do NOT open blister packs or
test nasal sprays before use.

Contains 5 blister packs (5 doses).
Each blister pack contains 1 nasal spray device.
1 device contains 1 dose (5 mg).

ATTENTION PHARMACIST:
The entire carton is to be dispensed as a unit. Dispense
the enclosed medication guide to the patient.

Check product expiration date before use.

PRINCIPAL DISPLAY PANEL - 15 mg Device Blister Pack Carton - 2 Doses

NDC 72252-515-04
Rx Only

VALTOCO®
(diazepam nasal spray) CIV

15 mg

FOR NASAL USE ONLY.

15 mg = 2 NASAL SPRAY DEVICES
DEVICES SPRAY ONE TIME ONLY

Do NOT open blister packs or
test nasal sprays before use.

This box contains 2 blister packs.
Each blister pack contains 2 nasal spray devices.
2 devices contains 1 dose (15 mg)

ATTENTION PHARMACIST:
The entire carton is to be dispensed as a unit. Dispense
the enclosed medication guide to the patient.

Check product expiration date before use.

PRINCIPAL DISPLAY PANEL - 15 mg Device Blister Pack Carton - 5 Doses

NDC 72252-515-10
Rx Only

VALTOCO®
(diazepam nasal spray) CIV

15 mg

FOR NASAL USE ONLY.

15 mg = 2 NASAL SPRAY DEVICES
DEVICES SPRAY ONE TIME ONLY

Do NOT open blister packs or
test nasal sprays before use.

Contains 5 blister packs (5 doses).
Each blister pack contains 2 nasal spray devices.
2 devices contain 1 dose (15 mg).

ATTENTION PHARMACIST:
The entire carton is to be dispensed as a unit. Dispense
the enclosed medication guide to the patient.

Check product expiration date before use.

PRINCIPAL DISPLAY PANEL - 10 mg Device Blister Pack Carton - 2 Doses

NDC 72252-510-02
Rx Only

VALTOCO®
(diazepam nasal spray) CIV

10 mg

FOR NASAL USE ONLY.

10 mg = 1 NASAL SPRAY DEVICE
DEVICE SPRAYS ONE TIME ONLY

Do NOT open blister packs or
test nasal sprays before use.

This box contains 2 blister packs.
Each blister pack contains 1 nasal spray device.
1 device contains 1 dose (10 mg)

ATTENTION PHARMACIST:
The entire carton is to be dispensed as a unit. Dispense
the enclosed medication guide to the patient.

Check product expiration date before use.

PRINCIPAL DISPLAY PANEL - 10 mg Device Blister Pack Carton - 5 Doses

NDC 72252-510-05
Rx Only

VALTOCO®
(diazepam nasal spray) CIV

10 mg

FOR NASAL USE ONLY.

10 mg = 1 NASAL SPRAY DEVICE
DEVICE SPRAYS ONE TIME ONLY

Do NOT open blister packs or
test nasal sprays before use.

Contains 5 blister packs (5 doses).
Each blister pack contains 1 nasal spray device.
1 device contains 1 dose (10 mg).

ATTENTION PHARMACIST:
The entire carton is to be dispensed as a unit. Dispense
the enclosed medication guide to the patient.

Check product expiration date before use.

PRINCIPAL DISPLAY PANEL - 20 mg Device Blister Pack Carton - 2 Doses

NDC 72252-520-04
Rx Only

VALTOCO®
(diazepam nasal spray) CIV

20 mg

FOR NASAL USE ONLY.

20 mg = 2 NASAL SPRAY DEVICES
DEVICES SPRAY ONE TIME ONLY

Do NOT open blister packs or
test nasal sprays before use.

This box contains 2 blister packs.
Each blister pack contains 2 nasal spray devices.
2 devices contain 1 dose (20 mg)

ATTENTION PHARMACIST:
The entire carton is to be dispensed as a unit. Dispense
the enclosed medication guide to the patient.

Check product expiration date before use.

PRINCIPAL DISPLAY PANEL - 20 mg Device Blister Pack Carton - 5 Doses

NDC 72252-520-10
Rx Only

VALTOCO®
(diazepam nasal spray) CIV

20 mg

FOR NASAL USE ONLY.

20 mg = 2 NASAL SPRAY DEVICES
DEVICES SPRAY ONE TIME ONLY

Do NOT open blister packs or
test nasal sprays before use.

Contains 5 blister packs (5 doses).
Each blister pack contains 2 nasal spray devices.
2 devices contain 1 dose (20 mg).

ATTENTION PHARMACIST:
The entire carton is to be dispensed as a unit. Dispense
the enclosed medication guide to the patient.

Check product expiration date before use.